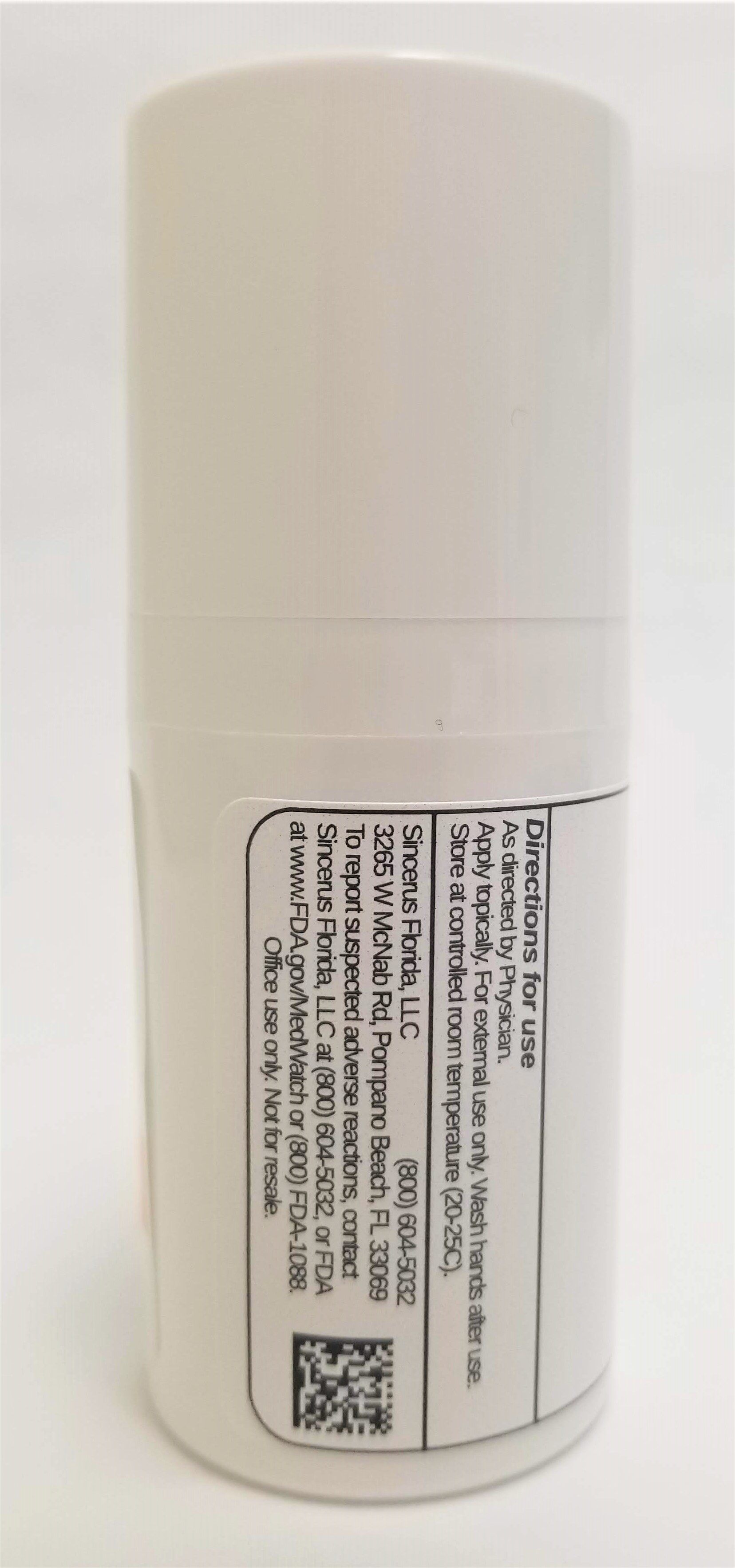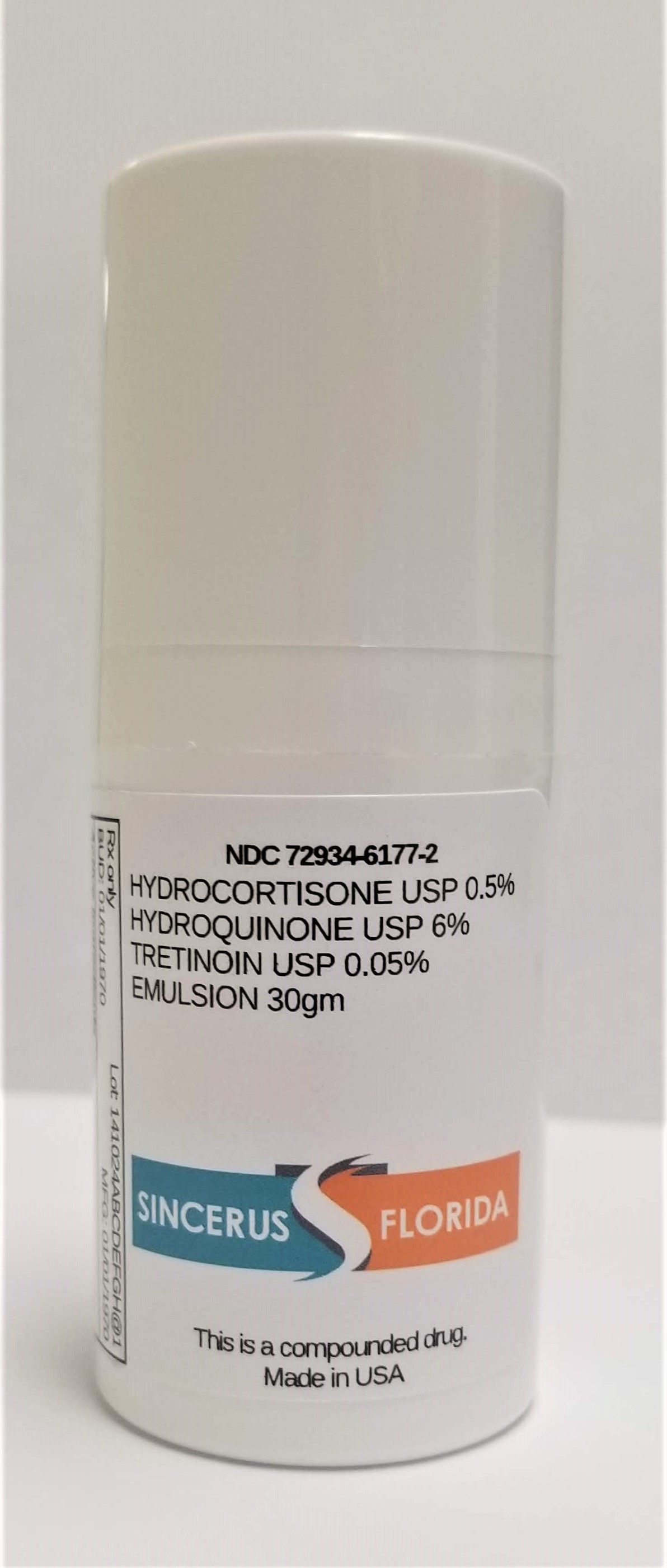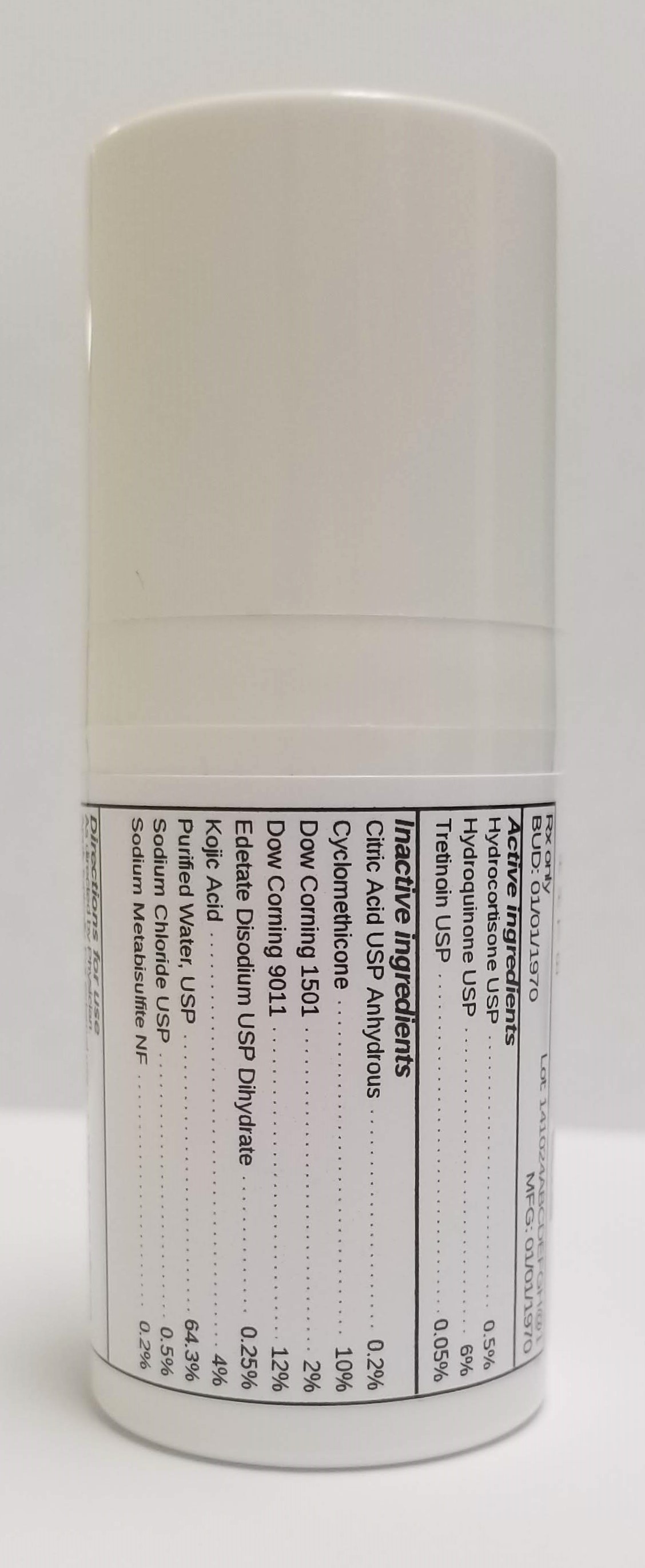 DRUG LABEL: HYDROCORTISONE 0.5% / HYDROQUINONE 6% / TRETINOIN 0.05%
NDC: 72934-6177 | Form: EMULSION
Manufacturer: Sincerus Florida, LLC
Category: prescription | Type: HUMAN PRESCRIPTION DRUG LABEL
Date: 20190522

ACTIVE INGREDIENTS: TRETINOIN 0.05 g/100 g; HYDROCORTISONE 0.5 g/100 g; HYDROQUINONE 6 g/100 g

HYDROCORTISONE 0.5% / HYDROQUINONE 6% / TRETINOIN 0.05%